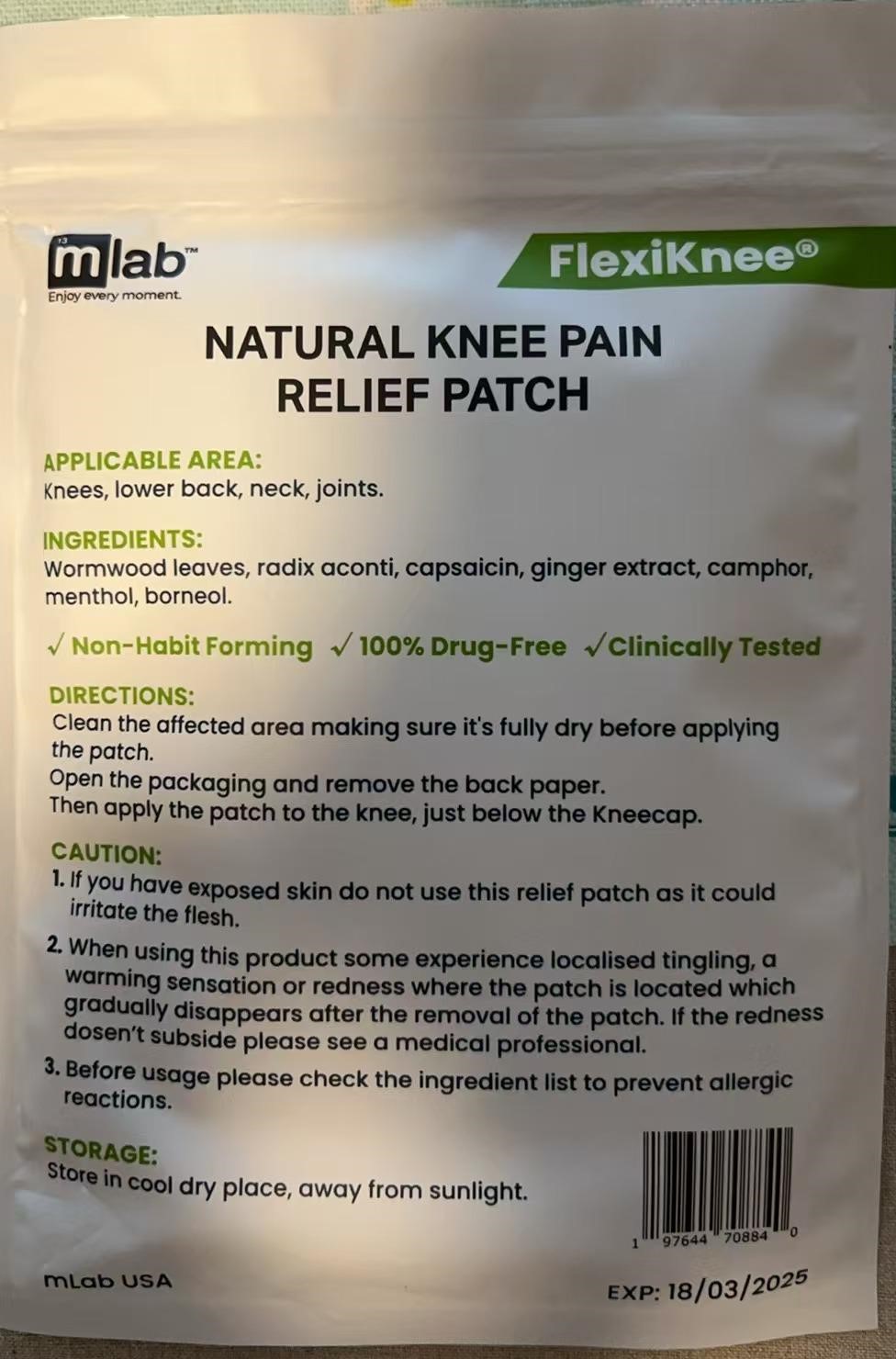 DRUG LABEL: NATURAL KNEE PAIN RELIEF
NDC: 84972-001 | Form: PATCH
Manufacturer: Nanyang Aihe Shanai Products Co., Ltd.
Category: otc | Type: HUMAN OTC DRUG LABEL
Date: 20241206

ACTIVE INGREDIENTS: WORMWOOD 25 g/100 g; ACONITUM NAPELLUS ROOT 14 g/100 g; CAPSAICIN 5 g/100 g; CAMPHOR (NATURAL) 3 g/100 g; GINGER 3 g/100 g
INACTIVE INGREDIENTS: BORNEOL; MENTHOL

84972-001-01

Active ingredients

Wormwood leaves, radix aconiti, Capsaicin, ginger extract, Camphor

Purpose

Relieves joint discomfort

Uses

alleviate neck, waist, leg and other joints discomfort of sub-healthy crowd.

Warning

Skin redness, hyperemia, ulceration, breakage are prohibited.
A burning sensation in the skin is normal.
This product does not replace drugs or medical devices treatment.

Directions

when needed, remove the backing paper and stick it on the painful part, once a day for 8-12 hours

Inactive ingredients

Menthol, Borneol